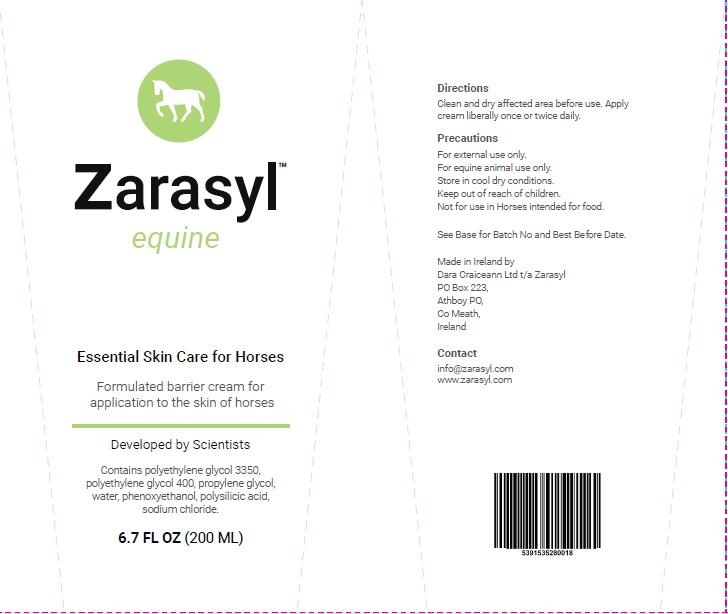 DRUG LABEL: Zarasyl
NDC: 86107-001 | Form: CREAM
Manufacturer: Dara Craiceann Limited
Category: animal | Type: OTC ANIMAL DRUG LABEL
Date: 20241021

ACTIVE INGREDIENTS: HYDRATED SILICA 0.074 g/200 mL
INACTIVE INGREDIENTS: Water; POLYETHYLENE GLYCOL 3350; POLYETHYLENE GLYCOL 400; PROPYLENE GLYCOL; PHENOXYETHANOL; SODIUM CHLORIDE

PRECAUTIONS

For external use only.
For equine animal use only.
Store in cool dry conditions.
Keep out of reach of children.
Not for use in Horses intended for food.

INSTRUCTIONS FOR USE

Clean and dry affected area before use. Apply cream liberally once or twice daily.

Package Label 08 Aug 2019.jpg